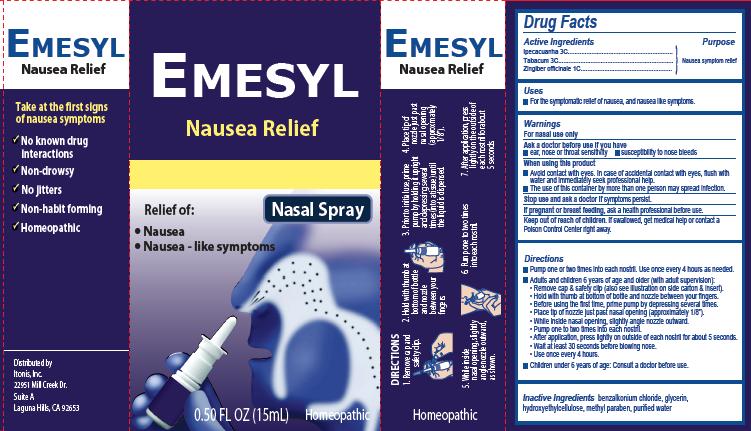 DRUG LABEL: Emesyl Nausea Relief
NDC: 59067-001 | Form: SPRAY
Manufacturer: Itonis, Inc.
Category: homeopathic | Type: HUMAN OTC DRUG LABEL
Date: 20181031

ACTIVE INGREDIENTS: IPECAC 3 [hp_C]/15 mL; TOBACCO LEAF 3 [hp_C]/15 mL; GINGER 1 [hp_C]/15 mL
INACTIVE INGREDIENTS: BENZALKONIUM CHLORIDE; GLYCERIN; HYDROXYETHYL CELLULOSE (100 MPA.S AT 2%); METHYLPARABEN; WATER

Emesyl Nausea Relief Nasal Spray

Active ingredients

Ipecacuanha 3C
Tabacum 3C
Zingiber officinale 1C

Purpose

Nausea symptom relief

Uses

For the symptomatic relief of nausea, and nausea like symptoms.

Warnings

For nasal use only

Ask a doctor before use if you have

- ear, nose or throat sensitivity
- susceptibility to nose bleeds

When using this product

- Avoid contact with eyes. In case of accidental contact with eyes, flush with water and immediately seek professional help.
- The use of this container by more than one person may spread infection.

Stop use and ask a doctor

if symptoms persist.

If pregnant or breast feeding,

ask a health professional before use.

Keep out of reach of children.

If swallowed, get medical help or contact a Poison Control Center right away.

Directions

- Pump one or two times into each nostril. Use once every 4 hours as needed.
- Adults and children 6 years of age and older (with adult supervision):
  - Remove cap & safety clip (also see illustration on side carton & insert).
  - Hold with thumb at bottom of bottle and nozzle between your fingers.
  - Before using the first time, prime pump by depressing several times.
  - Place tip of nozzle just past nasal opening (approximately 1/8”).
  - While inside nasal opening, slightly angle nozzle outward.
  - Pump one to two times into each nostril.
  - After application, press lightly on outside of each nostril for about 5 seconds.
  - Wait at least 30 seconds before blowing nose.
  - Use once every 4 hours
- Children under 6 years of age: Consult a doctor before use.

Inactive Ingredients

benzalkonium chloride, glycerin, hydroxyethylcellulose, methyl paraben, purified water

Principal Display Panel

Emesyl
Nausea Relief
Nasal Spray
Relief of:
•
Nausea
•
Nausea – like symptoms
0.50 FL OZ (15mL) Homeopathic
Take at the first signs of nausea symptoms

No known drug interactions
Non-drowsy

No jitters

Non-habit forming

Homeopathic
Distributed by:
Itonis, Inc.
22951 Mill Creek Dr.
Suite A
Laguna Hills, CA 92653

Product Package